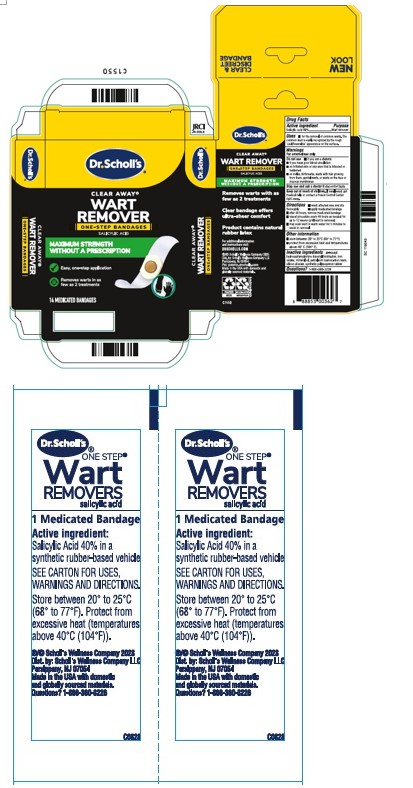 DRUG LABEL: One Step Wart Removers
NDC: 73469-6321 | Form: DISC
Manufacturer: Scholls Wellness Company LLC
Category: otc | Type: HUMAN OTC DRUG LABEL
Date: 20260113

ACTIVE INGREDIENTS: SALICYLIC ACID 0.4 g/1 g
INACTIVE INGREDIENTS: BROWN IRON OXIDE; SILICON DIOXIDE; MINERAL OIL; ANTIOXIDANT GS; TALC; WHITE PETROLATUM

90000442 One Step Wart Removers

Active Ingredient

Salicylic acid 40%

Purpose

Wart Remover

INDICATIONS AND USAGE

- for the removal of common wart. The common wart is easily recognized by the rough 'cauliflower-like' appearance on the surface

WARNINGS

For external use only

DO NOT USE

- if you are a diabetic
- if you have poor blood circulation
- on irritated skin or any aea that is infected or reddened
- on moles, birthmarks, warts with hair growing from them, genital warts, or warts on the face or mucous membranes

Stop use and ask a doctor if discomfort lasts

Keep out of reach of children.

If swallowed, get medical help or contact a Poison Control Center right away

DOSAGE AND ADMINISTRATION

- wash affected area and dry thoroughly
- apply medicated bandage
- after 48 hours, remove medicated bandage
- repeat procedure every 48 hours as needed for up to 14 days (until wart is removed)
- may soak wart in warm water for 5 minutes to assist in removal

STORAGE AND HANDLING

- store between 20° to 25°C (68° to 77°F)
- protect from excessive heat and temperatures above 40°C (140°F)

Inactive ingredients

Antioxidant (CAS 991-84-4), iron oxides, mineral oil, petroleum hydrocarbon resin, silicon dioxide, synthetic polyisoprene rubber, talc

Questions?

1-866-360-3226